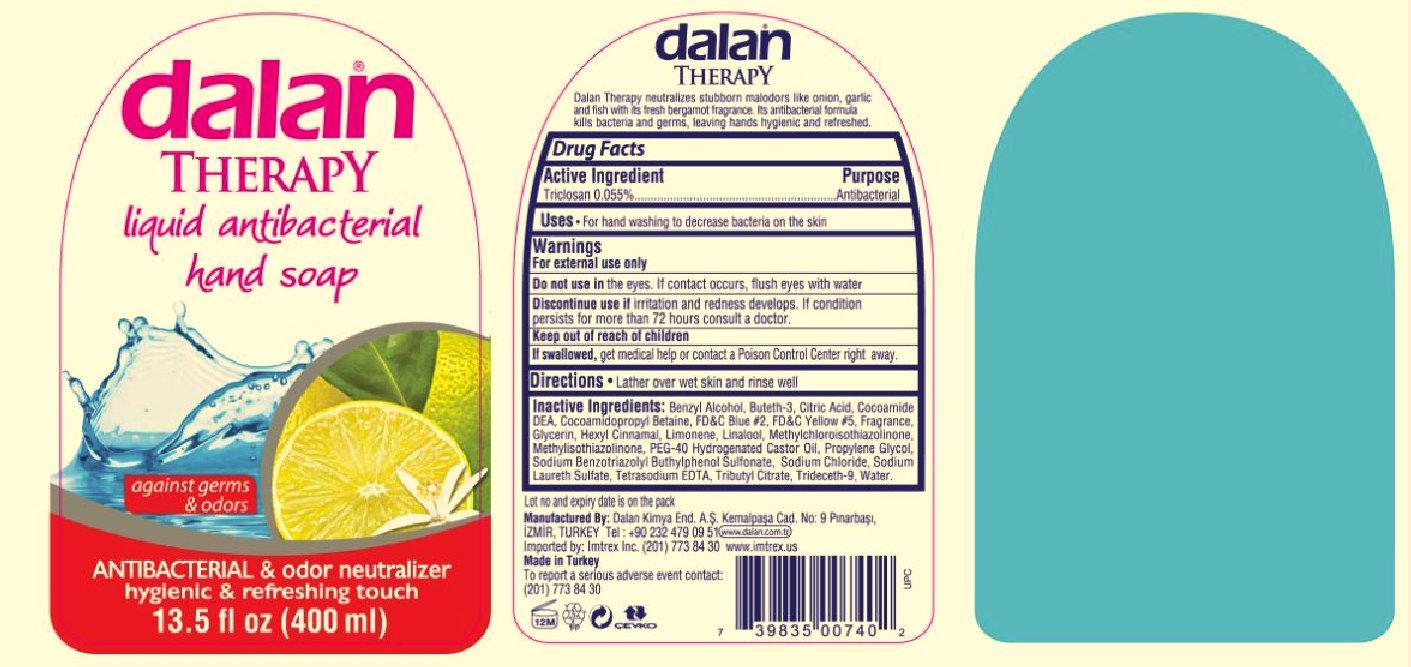 DRUG LABEL: dalan Therapy ANTIBACTERIAL and odor neutralizer
NDC: 51209-001 | Form: LIQUID
Manufacturer: Dalan Kimya Endustri A.S.
Category: otc | Type: HUMAN OTC DRUG LABEL
Date: 20140806

ACTIVE INGREDIENTS: TRICLOSAN 1 mg/1 mL
INACTIVE INGREDIENTS: BENZYL ALCOHOL; BUTETH-3; CITRIC ACID MONOHYDRATE; COCO DIETHANOLAMIDE; COCAMIDOPROPYL BETAINE; FD&C BLUE NO. 2; FD&C YELLOW NO. 5; GLYCERIN; .ALPHA.-HEXYLCINNAMALDEHYDE; LIMONENE, (+)-; LINALOOL, (+)-; METHYLCHLOROISOTHIAZOLINONE; METHYLISOTHIAZOLINONE; PEG-40 CASTOR OIL; PROPYLENE GLYCOL; SODIUM BENZOTRIAZOLYL BUTYLPHENOL SULFONATE; SODIUM CHLORIDE; SODIUM LAURETH SULFATE; EDETATE SODIUM; TRIBUTYL CITRATE; TRIDECETH-9; WATER

dalan Therapy liquid antibacterial hand soap ANTIBACTERIAL & odor neutralizer

Active Ingredient / Purpose

PURPOSE

Triclosan 0.055% ...... Antibacterial

Uses

For hand washing to decrease bacteria on the skin

Warnings

For external use only
Do not use in the eyes. If contact occurs, flush eyes with water
Discontinue use if irritation and redness develops. If condition persists for more than 72 hours consult a doctor.

Keep out of reach of children
If swallowed, get medical help or contact a Poison Control Center right away.

Directions

Lather over wet skin and rinse well

Inactive Ingredients:

Benzyl Alcohol, Buteth-3, Citric Acid, Cocoamide DEA, Cocoamidopropyl Betaine, FDandC Blue 2, FDandC Yellow5, Fragrance, Glycerin, Hexyl Cinnamal, Limonene, Linalool, Methylchloroisothiazolinone, Methylisothiazolinone, PEG-40 Hydrogenated Castor Oil, Propylene Glycol, Sodium Benzotriazolyl Buthylphenol Sulfonate, Sodium Chloride, Sodium Laureth Sulfate, Tetrasodium EDTA, Tributyl Citrate, Trideceth-9, Water.